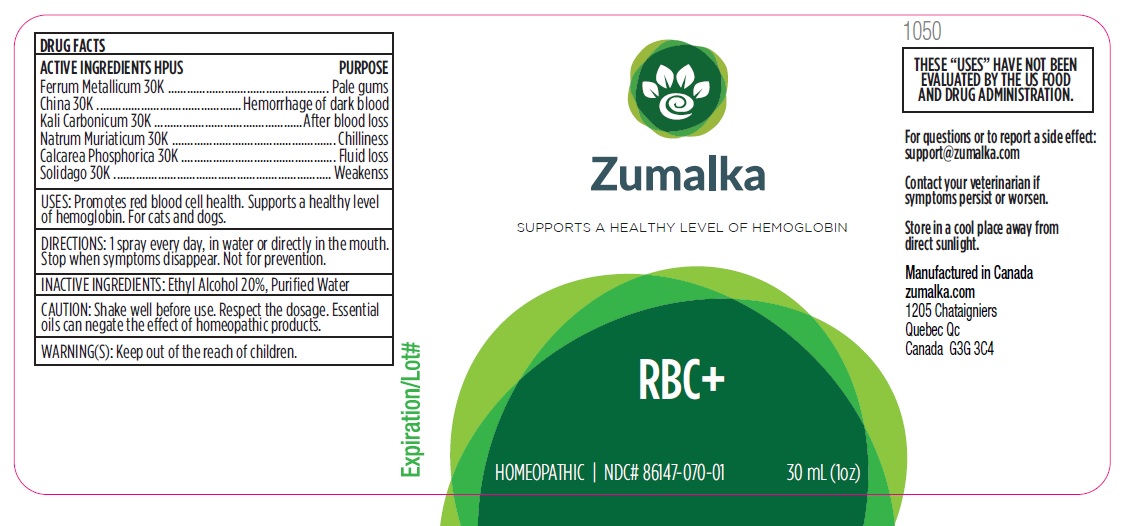 DRUG LABEL: RBC
NDC: 86147-070 | Form: LIQUID
Manufacturer: Groupe Cyrenne Inc.
Category: homeopathic | Type: OTC ANIMAL DRUG LABEL
Date: 20251120

ACTIVE INGREDIENTS: IRON 30 [kp_C]/30 mL; CINCHONA BARK 30 [kp_C]/30 mL; POTASSIUM CARBONATE 30 [kp_C]/30 mL; SODIUM CHLORIDE 30 [kp_C]/30 mL; TRIBASIC CALCIUM PHOSPHATE 30 [kp_C]/30 mL; SOLIDAGO VIRGAUREA FLOWERING TOP 30 [kp_C]/30 mL
INACTIVE INGREDIENTS: WATER; ALCOHOL

Active ingredients Purpose

Ferrum Metallicum 30k Pale gums

China 30k Hemorrhage of dark blood

Kali Carbonicum 30k After blood loss

Natrum Muriaticum 30k Chilliness

Calcarea Phosphorica 30k Fluid loss

Solidago 30k Weakenss

Uses

Promotes red blood cell health. Supports a healthy level of hemoglobin. For cats and dogs.

Warnings

Keep out of reach of children.

Direction

1 spray every day, in water or directly in the mouth. Stop when symptoms disappear. Not for prevention.

Inactive ingredients

Ethyl alcohol 20%, purified water

Cautions

Shake well before use. Respect the dosage. Essential oils can negate the effects of homeopathic products. Store in a cool place away from direct sunlight.